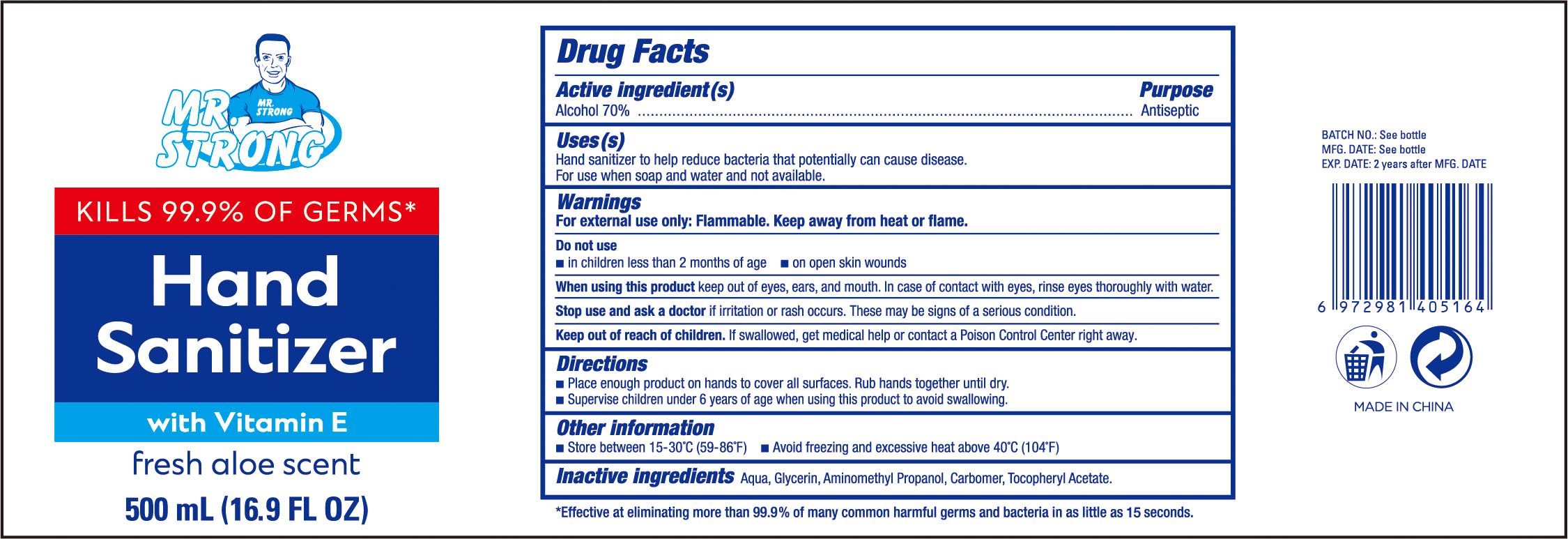 DRUG LABEL: hand sanitizer
NDC: 74834-001 | Form: GEL
Manufacturer: Y&R International (Wuhu) Industrial Limited
Category: otc | Type: HUMAN OTC DRUG LABEL
Date: 20200519

ACTIVE INGREDIENTS: ALCOHOL 70 mL/100 mL
INACTIVE INGREDIENTS: GLYCERIN; TOCOPHERYL RETINOATE; AMINOMETHYL PROPANEDIOL; CARBOMER 934; WATER

74834-001 Hand Sanitizer

ACTIVE INGREDIENT

Alcohol 70%

Purpose

Antiseptic

Use

Hand sanitizer to help reduce bacteria that potentially can cause disease.

For use when soap and water and not available.

WARNINGS

For external use only: Flammable. Keep away from heat or flame.

Do not use

■ in children less than 2 months of age ■on open skin wounds

When using this product keep out of eyes, ears, and mouth. In case of contact with eyes, rinse eyes thoroughly with water.

Stop use and ask a doctor if irritation or rash occurs. These may be signs of a serious condition.

Keep out of reach of children. If swallowed,
get medicalhelp or contact a Poison Control Center.

Directions

■Place enough product on hands to cover all surfaces. Rub hands together until dry.

■Supervise children under 6 years of age when using this product to avoid swallowing.

Inactive ingredients

Aqua, Glycerin, Aminomethyl Propanol, Carbomer, Tocopheryl Acetate